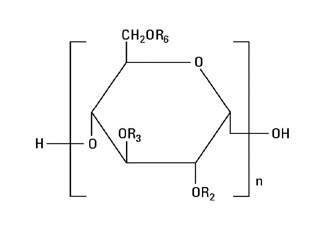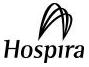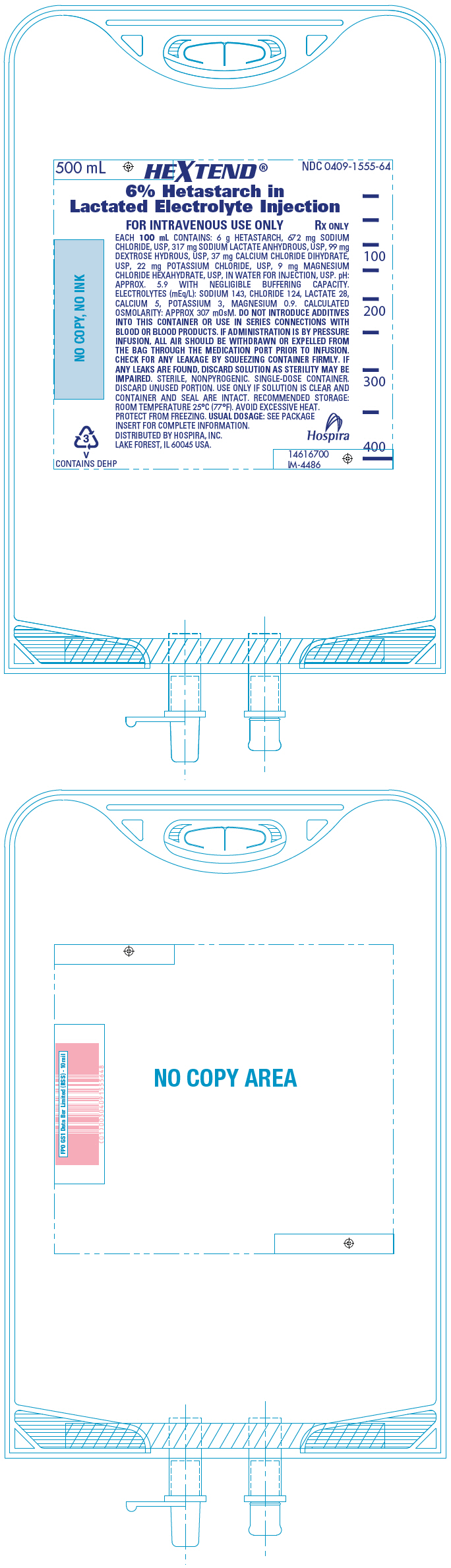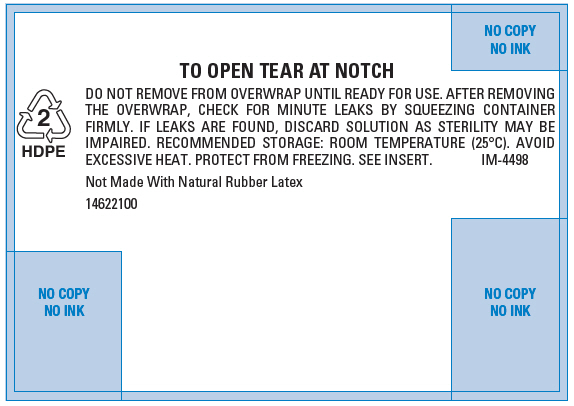 DRUG LABEL: Hextend
NDC: 0409-1555 | Form: INJECTION, SOLUTION
Manufacturer: Hospira, Inc.
Category: prescription | Type: HUMAN PRESCRIPTION DRUG LABEL
Date: 20251230

ACTIVE INGREDIENTS: HETASTARCH 6 g/100 mL
INACTIVE INGREDIENTS: SODIUM CHLORIDE; SODIUM LACTATE; DEXTROSE MONOHYDRATE; CALCIUM CHLORIDE; POTASSIUM CHLORIDE; MAGNESIUM CHLORIDE; WATER

HEXTEND® Rx only

6% Hetastarch in Lactated Electrolyte Injection

Flexible Plastic Container

WARNING: MORTALITY; KIDNEY INJURY; COAGULOPATHY

- Use of hydroxyethyl starch (HES) products, including HEXTEND®, increases risk of
  - Mortality
  - Kidney injury
  - Coagulopathy

DO NOT use HES products, including HEXTEND®, unless adequate alternative treatment is unavailable.

DESCRIPTION

HEXTEND® (6% Hetastarch in Lactated Electrolyte Injection) is a sterile, nonpyrogenic solution for intravenous administration. The composition, pH, and osmolarity are given in Table 1 and the electrolyte composition in Table 2.

Table 1
Each 100 mL contains
Hetastarch | 6 g
Sodium Chloride, USP | 672 mg
Sodium Lactate Anhydrous, USP | 317 mg
Dextrose Hydrous, USP | 99 mg
Calcium Chloride Dihydrate, USP | 37 mg
Potassium Chloride, USP | 22 mg
Magnesium Chloride Hexahydrate, USP | 9 mg
Water for Injection, USP | qs
pH: approximately 5.9 with negligible buffering capacity
Calculated Osmolarity: approximately 307 mOsM

Table 2
Concentration of Electrolytes (mEq/L)
Sodium | 143
Chloride | 124
Lactate | 28
Calcium | 5
Potassium | 3
Magnesium | 0.9

HEXTEND (6% Hetastarch in Lactated Electrolyte Injection) is an artificial colloidal solution, pharmacologically classified as a plasma volume expander, and is intended to support oncotic pressure as well as provide electrolytes.

HEXTEND contains high molecular weight hetastarch at a concentration of 6% as an oncotic agent to permit retention of intravascular fluid until the hetastarch is replaced by blood proteins. Hetastarch is an artificial colloid derived from a waxy starch composed almost entirely of amylopectin. Hydroxyethyl ether groups are introduced into the glucose units of the starch, and the resultant material is hydrolyzed to yield a product with a molecular weight suitable for use as a plasma volume expander. Hetastarch is characterized by its molar substitution and also by its molecular weight. The molar substitution is approximately 0.75 which means hetastarch has an average of approximately 75 hydroxyethyl groups for every 100 glucose units. The weight average molecular weight is approximately 670,000 with a range of 450,000 to 800,000 and with at least 80% of the polymer units falling within the range of 20,000 to 2,500,000. Hydroxyethyl groups are attached by ether linkage primarily at C-2 of the glucose unit and to a lesser extent at C-3 and C-6. The polymer resembles glycogen, and the polymerized D-glucose units are joined primarily by α-1,4 linkages with occasional α-1,6 branching linkages. The degree of branching is approximately 1:20 which means that there is an average of approximately one α-1,6 branch for every 20 glucose monomer units.

The chemical name for hetastarch is hydroxyethyl starch.

The structural formula is as follows:

Amylopectin derivative in which R2 and R3 are H or CH2CH2OH and R6 is H, CH2CH2OH, or a branching point in the starch polymer connected through an α-1,6 link to additional D-glucopyranosyl units

HEXTEND is a clear, pale yellow to amber solution. Exposure to prolonged adverse storage conditions may result in a change to a turbid deep brown or the formation of a crystalline precipitate. Do not use the solution if these conditions are evident.

HEXTEND is formulated with normal physiological levels of calcium. Calcium chloride in water dissociates to provide calcium (Ca^++) and chloride (Cl^-) ions. These are the normal constituents of the body fluids and are dependent on various physiologic mechanisms for maintenance of balance between intake and output. Approximately 80% of body calcium is excreted in the feces as insoluble salts; urinary excretion accounts for the remaining 20%.

HEXTEND also contains normal physiological levels of sodium. Additionally, chloride is present at levels closer to those normally found in blood than in plasma expanders in 0.9% Sodium Chloride Injection. Sodium chloride in water dissociates to provide sodium (Na^+) and chloride (Cl^-) ions. Sodium (Na^+) is the principal cation of the extracellular fluid and plays a large part in the therapy of fluid and electrolyte disturbances. Chloride (Cl^-) has an integral role in buffering action when oxygen and carbon dioxide exchange occurs in the red blood cells. The distribution and excretion of sodium (Na^+) and chloride (Cl^-) are largely under the control of the kidneys, which maintain a balance between intake and output.

HEXTEND also contains slightly lower than normal physiological levels of potassium and magnesium. Potassium chloride in water dissociates to provide potassium (K^+) and chloride (Cl^-) ions. Potassium is found in low concentrations in plasma and extracellular fluids (3.5 to 5.0 mEq/L in a healthy adult). It is the most abundant cation within the body's cells (160 mEq/L of intracellular water). Potassium plays an important role in electrolyte balance. Normally about 80 to 90% of the potassium intake is excreted in the urine with the remainder in the stools and, to a small extent, in the perspiration. The kidney does not conserve potassium well so that during fasting or in patients on a potassium-free diet, potassium loss from the body continues thereby resulting in potassium depletion.

Magnesium chloride in water dissociates to provide magnesium (Mg^++) and chloride (Cl^-). Magnesium is largely an intracellular ion with low concentrations (1.5 to 2.5 mEq/L) found in plasma.

Dextrose is included in the formulation. Solutions containing carbohydrate in the form of dextrose yield blood glucose, provide calories, and may also aid in minimizing liver glycogen depletion thereby exerting a protein sparing effect. Dextrose injected parenterally undergoes oxidation to carbon dioxide and water.

Lactate is provided at 28 mEq/L. Sodium lactate in water dissociates to provide sodium (Na^+) and lactate (C3H5O3^-) ions. The lactate anion provides an alkaline effect resulting from simultaneous removal of lactate and hydrogen ions by the liver. In the liver, the lactate is metabolized to glycogen, which is ultimately converted to carbon dioxide and water by oxidative metabolism.

The lactate anion acts as a source (alternate) of bicarbonate when normal production and utilization of lactic acid is not impaired as a result of disordered lactate metabolism. Since metabolic conversion is dependent on the integrity of cellular oxidative processes, lactate may be inadequate or ineffective as a source of bicarbonate in patients suffering from acidosis associated with shock or other disorders involving reduced perfusion of body tissues. When oxidative activity is intact, one to two hours is required for metabolism of lactate.

Water is an essential constituent of all body tissues and accounts for approximately 70% of total body weight. The average normal adult daily requirement ranges from 2 to 3 L (1.0 to 1.5 L each for insensible water loss by perspiration and urine production). Water balance is maintained by various regulatory mechanisms. Water distribution depends primarily on the concentration of electrolytes in the body compartments, and sodium (Na^+) plays a major role in maintaining physiological equilibrium.

The flexible plastic container is fabricated from a specially formulated polyvinylchloride. Solutions in contact with the plastic container may leach out certain chemical components from the plastic in very small amounts; however, biological testing was supportive of the safety of the plastic container materials. The container solution unit is a closed system and is not dependent upon entry of external air during administration. The container is overwrapped to provide protection from the physical environment and to provide an additional moisture barrier when necessary.

The closure system has two ports; the one for the administration set has a tamper evident plastic protector.

CLINICAL PHARMACOLOGY

The plasma volume expansion produced by HEXTEND approximates that produced by 6% Hetastarch in 0.9% Sodium Chloride Injection and the plasma volume expansion of 6% Hetastarch in 0.9% Sodium Chloride Injection in turn approximates that of 5% Albumin (Human).^1-4 In randomized, double-blind studies of HEXTEND versus control (6% Hetastarch in 0.9% Sodium Chloride Injection) for the treatment of hypovolemia in elective surgery, 60 patients were infused with a mean of 1596 mL of HEXTEND and 59 patients were infused with a mean of 1428 mL of 6% Hetastarch in 0.9% Sodium Chloride Injection without any serious related adverse events. 59% of the HEXTEND patients and 59% of the control patients required packed red blood cells and other blood-derived products either intraoperatively or postoperatively.

Intravenous infusion of 6% Hetastarch in 0.9% Sodium Chloride Injection results in expansion of plasma volume that decreases over the succeeding 24 to 36 hours. The degree of plasma volume expansion and improvement in hemodynamic state depend upon the patient's intravascular status. When administered intravenously, HEXTEND provides sources of water and electrolytes. Its electrolyte content resembles that of the principal ionic constituents of normal plasma.

Hetastarch molecules below 50,000 molecular weight are rapidly eliminated by renal excretion. A single dose of approximately 500 mL of 6% Hetastarch in 0.9% Sodium Chloride Injection (approximately 30 g) results in elimination in the urine of approximately 33% of the dose within 24 hours. This is a variable process but generally results in an intravascular hetastarch concentration of less than 10% of the total dose injected by two weeks. A study of the biliary excretion of hetastarch in 10 healthy males accounted for less than 1% of the dose over a 14 day period. The hydroxyethyl group is not cleaved by the body but remains intact and attached to glucose units when excreted. Significant quantities of glucose are not produced as hydroxyethylation prevents complete metabolism of the smaller polymers.

INDICATIONS AND USAGE

HEXTEND (6% Hetastarch in Lactated Electrolyte Injection) is indicated in the treatment of hypovolemia when plasma volume expansion is desired in settings where adequate alternative treatment is unavailable. It is not a substitute for blood or plasma.

CONTRAINDICATIONS

Do not use HES products, including HEXTEND, unless adequate alternative treatment is unavailable.

WARNINGS AND PRECAUTIONS

- Increased risk of mortality and acute kidney injury (AKI) in critically ill patients, including patients with sepsis; surgical patients; and blunt trauma patients
- Avoid use in patients with pre-existing renal dysfunction
- Discontinue use of HEXTEND at the first sign of renal injury
- Continue to monitor renal function for at least 90 days as use of renal replacement therapy (RRT) has been reported up to 90 days after administration of HES products
- Monitor the coagulation status of surgery patients, as excess bleeding has been reported with HES solutions in this population. Discontinue use of HEXTEND at the first sign of coagulopathy
- Monitor liver function in patients receiving HES products, including HEXTEND

Solutions containing calcium should not be administered simultaneously with blood through the same administration set because of the likelihood of coagulation.

Life threatening anaphylactic/anaphylactoid reactions have been rarely reported with solutions containing hetastarch; death has occurred, but a causal relationship has not been established. Patients who develop severe anaphylactic/anaphylactoid reactions may need continued supportive care until symptoms have resolved.

Hypersensitivity reactions can occur even after solutions containing hetastarch have been discontinued.

Solutions which contain potassium should be used with great care, if at all, in patients with hyperkalemia and severe renal failure and in situations in which potassium retention is present.

Solutions containing sodium ions should be used with great care, if at all, in patients with congestive heart failure and severe renal insufficiency and in clinical states in which edema with sodium retention occurs.

In patients with diminished renal function, administration of solutions containing sodium or potassium ions may result in sodium or potassium retention.

Solutions containing lactate ions should be used with great care in patients with metabolic or respiratory alkalosis. The administration of lactate ions should be performed with great care when dealing with conditions in which an increased level or an impaired utilization of these ions occurs, such as severe hepatic insufficiency.

DO NOT USE IN LEUKAPHERESIS.

Usage in Plasma Volume Expansion

Large volumes of isotonic solutions containing 6% hetastarch (HEXTEND or 6% Hetastarch in 0.9% Sodium Chloride Injection) may transiently alter the coagulation mechanism due to hemodilution and a direct inhibitory action on Factor VIII. Hemodilution by isotonic solutions containing 6% hetastarch may also result in a 24 hour decline of total protein, albumin, and fibrinogen levels and in transient prolongation of prothrombin, activated partial thromboplastin, clotting, and bleeding times.

Increased bleeding has been reported in patients undergoing open heart surgery in association with cardiopulmonary bypass following the use of 6% Hetastarch in 0.9% Sodium Chloride Injection.^5,6 Although the electrolyte content of HEXTEND resembles that of the principal ionic constituents of normal plasma, its 6% Hetastarch component is identical to that of 6% Hetastarch in 0.9% Sodium Chloride Injection and has a direct inhibitory action on Factor VIII. There are no retrospective studies similar to those with 6% Hetastarch in 0.9% Sodium Chloride Injection that compare HEXTEND to albumin in cardiopulmonary bypass surgery nor have any adequate and well-controlled clinical studies been performed.

Hematocrit may be decreased and plasma proteins diluted excessively by administration of large volumes of isotonic solutions containing 6% hetastarch. Administration of packed red cells, platelets, and fresh frozen plasma should be considered if excessive dilution occurs.

In randomized, controlled, comparative studies of 6% Hetastarch in 0.9% Sodium Chloride Injection (n = 92) and Albumin (n = 85) in surgical patients, no patient in either treatment group had a bleeding complication and no significant difference was found in the amount of blood loss between the treatment groups.^1-4

HEXTEND has not been adequately evaluated to establish its safety in situations other than treatment of hypovolemia in elective surgery. In some cases, the use of isotonic solutions containing 6% hetastarch has been associated with coagulation abnormalities in conjunction with an acquired, reversible von Willebrand's-like syndrome and/or Factor VIII deficiency when used over a period of days. Replacement therapy should be considered if a severe Factor VIII or von Willebrand deficiency is identified. If a coagulopathy develops, it may take several days to resolve. Certain conditions may affect the safe use of isotonic solutions containing 6% hetastarch on a chronic basis. For example, in patients with subarachnoid hemorrhage where an isotonic solution containing 6% hetastarch is used repeatedly over a period of days for the prevention of cerebral vasospasm, significant clinical bleeding may occur. Intracranial bleeding resulting in death has been reported with the use of 6% Hetastarch in 0.9% Sodium Chloride Injection.^7

The possibility of circulatory overload should be kept in mind. Caution should be used when the risk of pulmonary edema and/or congestive heart failure is increased. Special care should be exercised in patients who have impaired renal clearance since this is the principal way in which hetastarch is eliminated and in clinical states in which edema with sodium retention occurs.

Indirect bilirubin levels of 8.3 mg/L (normal 0.0-7.0 mg/L) have been reported in 2 out of 20 normal subjects who received multiple infusions of 6% Hetastarch in 0.9% Sodium Chloride Injection. Total bilirubin was within normal limits at all times; indirect bilirubin returned to normal by 96 hours following the final infusion. The significance, if any, of these elevations is not known; however, caution should be observed before administering isotonic solutions containing 6% hetastarch to patients with a history of liver disease.

If a hypersensitivity effect occurs, administration of the drug should be discontinued and appropriate treatment and supportive measures should be undertaken (see WARNINGS AND PRECAUTIONS).

Caution should be used when administering solutions containing hetastarch to patients allergic to corn because such patients can also be allergic to hetastarch.

HEXTEND should be used with caution in patients who have been anticoagulated with other drugs that negatively influence the coagulation system.

Clinical evaluation and periodic laboratory determinations are necessary to monitor changes in fluid balance, electrolyte concentrations, acid-base balance, and coagulation parameters during prolonged parenteral therapy or whenever the condition of the patient warrants such evaluation.

Solutions containing dextrose should be used with caution in patients with known subclinical or overt diabetes mellitus.

Caution must be exercised in the administration of parenteral fluids, especially those containing sodium ions, to patients receiving corticosteroids or corticotropin.

Potassium containing solutions should be used with caution in the presence of cardiac disease, particularly in digitalized patients or in the presence of renal disease.

Solutions containing lactate ions should be used with caution as excess administration may result in metabolic alkalosis.

Elevated serum amylase levels may be observed temporarily following administration of solutions containing hetastarch although no association with pancreatitis has been demonstrated. Serum amylase levels cannot be used to assess or to evaluate for pancreatitis for 3-5 days after administration of solutions containing hetastarch. Elevated serum amylase levels persist for longer periods of time in patients with renal impairment. Solutions containing hetastarch have not been shown to increase serum lipase.

One report suggests that in the presence of renal glomerular damage, larger molecules of hetastarch can leak into the urine and elevate the specific gravity. The elevation of specific gravity can obscure the diagnosis of renal failure.

Hetastarch is not eliminated by hemodialysis. The utility of other extracorporeal elimination techniques has not been evaluated.

If administration is by pressure infusion, all air should be withdrawn or expelled from the bag through the medication port prior to infusion.

Carcinogenesis, Mutagenesis, Impairment of Fertility

Long-term studies of animals have not been performed to evaluate the carcinogenic potential of hetastarch.

Teratogenic Effects

6% Hetastarch in 0.9% Sodium Chloride Injection has been shown to have an embryocidal effect on New Zealand rabbits when given intravenously over the entire organogenesis period in a daily dose 1/2 times the maximum recommended therapeutic human dose (1500 mL) and on BD rats when given intraperitoneally, from the 16th to the 21st day of pregnancy, in a daily dose 2.3 times the maximum recommended therapeutic human dose. When 6% Hetastarch in 0.9% Sodium Chloride Injection was administered to New Zealand rabbits, BD rats, and Swiss mice with intravenous daily doses of 2 times, 1/3 times, and 1 times the maximum recommended therapeutic human dose, respectively, over several days during the period of gestation, no evidence of teratogenicity was evident. There are no adequate and well controlled studies in pregnant women. HEXTEND should be used during pregnancy only if the potential benefit justifies the potential risk to the fetus.

Nursing Mothers

It is not known whether hetastarch is excreted in human milk. Because many drugs are excreted in human milk, caution should be exercised when HEXTEND is administered to a nursing woman.

Pediatric Use

The safety and effectiveness of HEXTEND in pediatric patients have not been established. Adequate, well-controlled clinical trials to establish the safety and effectiveness of HEXTEND in pediatric patients have not been conducted. However, in one small double-blind study, 47 infants, children, and adolescents (ages 1 year to 15.5 years) scheduled for repair of congenital heart disease with moderate hypothermia were randomized to receive either 6% Hetastarch in 0.9% Sodium Chloride Injection or Albumin as a postoperative volume expander during the first 24 hours after surgery. Thirty-eight children required colloid replacement therapy, of which 20 children received 6% Hetastarch in 0.9% Sodium Chloride Injection. No differences were found in the coagulation parameters or in the amount of replacement fluids required in the children receiving 20 mL/kg or less of either colloid replacement therapy. In children who received greater than 20 mL/kg of 6% Hetastarch in 0.9% Sodium Chloride Injection, an increase in prothrombin time was demonstrated (p = 0.006).^8 There were no neonates included in this study.

Geriatric Use

Of the total number of patients in clinical trials of HEXTEND (n=119), 30% were 65 or older while 12% were 70 or older. Other reported experience with 6% Hetastarch in 0.9% Sodium Chloride Injection has not identified differences in responses between elderly and younger patients, but greater sensitivity of some older individuals cannot be ruled out.

This drug is known to be substantially excreted by the kidney, and the risk of toxic reactions to this drug may be greater in patients with impaired renal function. Because elderly patients are more likely to have decreased renal function, care should be taken in dose selection, and it may be useful to monitor renal function.

ADVERSE REACTIONS

Serious adverse reactions reported in postmarketing clinical trials include increased mortality and AKI (including need for RRT) in critically ill subjects, including subjects with sepsis, and surgical subjects. Clinical trials have also shown increased mortality and AKI in blunt trauma subjects. Increased coagulopathy was reported in surgical subjects.

In clinical trials comparing the plasma volume expanding properties of HEXTEND (n=60) with those of 6% Hetastarch in 0.9% Sodium Chloride Injection (n=59), there were no significant differences in the number of adverse or serious adverse events between the two groups.

Reported adverse reactions with isotonic solutions containing 6% hetastarch include:

General

Hypersensitivity (see WARNINGS AND PRECAUTIONS).

Death, life-threatening anaphylactic/anaphylactoid reactions, cardiac arrest, ventricular fibrillation, severe hypotension, non-cardiac pulmonary edema, laryngeal edema, bronchospasm, angioedema, wheezing, restlessness, tachypnea, stridor, fever, chest pain, bradycardia, tachycardia, shortness of breath, chills, urticaria, pruritus, facial and periorbital edema, coughing, sneezing, flushing, erythema multiforme, and rash.

Cardiovascular

Circulatory overload, congestive heart failure, and pulmonary edema (see WARNINGS AND PRECAUTIONS).

Hematologic

Intracranial bleeding, bleeding and/or anemia due to hemodilution (see WARNINGS AND PRECAUTIONS) and/or Factor VIII deficiency, acquired von Willebrand's-like syndrome, and coagulopathy including rare cases of disseminated intravascular coagulopathy and hemolysis. With extensive clinical use of 6% Hetastarch in 0.9% Sodium Chloride Injection, rare cases of disseminated intravascular coagulopathy and hemolysis have been observed.

Metabolic

Metabolic acidosis.

Other

Vomiting, peripheral edema of the lower extremities, submaxillary and parotid glandular enlargement, mild influenza-like symptoms, headaches, and muscle pains. Hydroxyethyl starch-associated pruritus has been reported in some patients with deposits of hydroxyethyl starch in peripheral nerves.

CLINICAL STUDIES

Because clinical trials are conducted under widely varying conditions, adverse reaction rates observed in the clinical trials of a drug cannot be directly compared to rates in the clinical trials of another drug and may not reflect the rates observed in clinical practice. (Note: All of the studies listed below used licensed HES products except for reference 9.)

A randomized controlled trial (N=804) in severe sepsis patients using an HES product not licensed in the U.S. reported increased mortality (relative risk, 1.17; 95% CI, 1.01 to 1.36; p=0.03) and RRT (relative risk, 1.35; 95% CI, 1.01 to 1.80; p=0.04) in the HES treatment arm.^9

Another randomized controlled trial (N=196) in severe sepsis patients reported no difference in mortality (relative risk, 1.20; 95% CI, 0.83 to 1.74; p=0.33) and a trend for RRT (relative risk, 1.83; 95% CI, 0.93 to 3.59; p=0.06) in HES patients.^10

A randomized controlled trial (N=7000) in a heterogeneous population of ICU patients reported no difference in mortality (relative risk, 1.06; 95% CI, 0.96 to 1.18; p=0.26) but increased use of RRT (relative risk, 1.21; 95% CI, 1.00 to 1.45; p=0.04 in HES patients.^11

In a retrospective study of adult patients (N=1442) undergoing pulmonary or esophageal surgery who were prophylactically fluid-restricted during the procedure, 74 developed AKI (5.1%) within the first 72 hours postoperatively. Fluid restriction neither increased nor was a risk factor for AKI. AKI occurred more often when HES products were administered to patients with decreased renal function or having >2 risk factors with normal renal function, whereas restriction of crystalloid was unrelated to AKI, regardless of preoperative renal function.^12

In a retrospective case series of high-risk adult vascular surgery patients (N=796) receiving fluid therapy during a vascular surgery procedure, logistic regression analysis using prespecified confounding variables or suspected risk factors for AKI that showed intraoperative administration of an HES product was associated with increased likelihood of 30-day mortality and need for RRT, compared with use of crystalloids alone.^13

In a retrospective study of adult patients undergoing elective noncardiac surgery, patients (N=14,680) receiving an HES product and crystalloid were propensity-matched with patients (N=14,680) receiving only crystalloid. After controlling for potential confounding variables, odds of experiencing AKI of severe intensity with HES was 21% greater than with crystalloid alone. In addition, AKI risk increased as a function of HES volume.^14

In a prospective observational study assessing the impact of HES products on recipient renal graft outcomes in brain-dead organ donors, data were obtained on 986 kidneys transplanted from 529 donors. Kidneys from donors who received HES had a higher rate of delayed graft function in recipient subjects (41% versus 31%). After accounting for the propensity of donors to receive HES products, HES product administration was independently associated with an increased risk of delayed graft function in recipients. A dose-response relationship also was evident.^15

In a randomized, controlled trial of adult subjects (N=33) undergoing elective cystectomy comparing an HES product versus lactated Ringer's, administration of HES reduced clot strength (Maximum Amplitude; p<0.001) and increased blinded evaluation of perioperative blood loss by more than 50% (2181 mL versus 1370 mL, respectively; p=0.04). There was no significant between-group difference with respect to frequency of reoperation or length of hospital stay.^16

In a prospective, sequential, observational study in adult subjects undergoing open heart surgery in association with cardiopulmonary bypass, fluid therapy using only an HES product (2004–2006, N=2137), 4% gelatin (2006–2008, N=2324) and crystalloids (N=2017, 2008–2010) led to increased need for renal replacement therapy after HES and gelatin, compared with crystalloid. Propensity score stratification confirmed greater use of RRT in the HES and gelatin periods compared to the crystalloid period. Fluid intake was higher in the crystalloid group only during the first 20 hours.^17

In a retrospective observational study, 606 adult patients underwent open heart surgery in association with cardiopulmonary bypass. Until July 2013 they received an HES product (N=247) both as pump prime (1500 mL) and intraoperative fluid replacement (1000 mL), but only crystalloid (N=359) from August 2013 onward. The frequency (percent) of postoperative AKI was higher in patients receiving HES (N=53; 21.5%) than those receiving crystalloid (N=34; 9.5%). Surgical revision for rebleeding also was higher for HES (N=11; 4.6%) than for crystalloid (N=5; 1.4%).^18

In a meta-analysis of RCTs (n=15) in adult subjects (N=4409) undergoing surgery who received an HES product, significantly more HES subjects (83/2157; 3.8%) than controls (56/2252; 2.5%) underwent RRT (relative risk, 1.44; 95% CI, 1.04, 2.01).^19

In a retrospective observational study of adult blunt and penetrating trauma patients, use of an HES product was a significant independent predictor of AKI after blunt trauma, but not penetrating trauma, in multiple logistic regression analysis. In separate logistic regression models, HES also was a significant predictor of mortality after blunt trauma but not penetrating trauma.^20

In a retrospective observational study of severely injured adult blunt (89%) and penetrating (11%) trauma patients (N=413) admitted to the ICU, 103 patients developed AKI within the first week of ICU admission. AKI was associated with increased 30-day (17.5% versus 5.8%, AKI versus non-AKI cohorts, respectively) and 1-year mortality (26.2% versus 7.1%). Univariate and multivariable regression analyses of prespecified risk factors for AKI found that volume loading using an HES product was independently associated with postinjury AKI within the first 24 hours.^21

Postmarketing Experience

Because adverse reactions are reported voluntarily post-approval from a population of uncertain size, it is not always possible to reliably estimate the frequency of these reactions or establish a causal relationship to product exposure.

DOSAGE AND ADMINISTRATION

Dosage for Acute Use in Plasma Volume Expansion

HEXTEND is administered by intravenous infusion only. Total dosage and rate of infusion depend upon the amount of blood or plasma lost and the resultant hemoconcentration as well as age, weight, and clinical condition of the patient.

Adults: The amount usually administered is 500 to 1000 mL. Doses of more than 1500 mL per day for the typical 70 kg patient (approximately 20 mL per kg of body weight) are usually not required although doses of isotonic solutions containing 6% hetastarch up to 1500 mL have been used during major surgery generally without a need for blood or blood products. Volumes in excess of 1500 mL per day have been used where severe blood loss has occurred although generally only in conjunction with the administration of blood and blood products (see WARNINGS AND PRECAUTIONS).

Pediatric Patients: Adequate, well controlled clinical trials to establish the safety and effectiveness of HEXTEND in pediatric patients have not been conducted (see WARNINGS AND PRECAUTIONS, Pediatric Use).

General Recommendations

Do not use plastic container in series connection.

If administration is controlled by a pumping device, care must be taken to discontinue pumping action before the container runs dry or air embolism may result.

This solution is intended for intravenous administration using sterile equipment. It is recommended that intravenous administration apparatus be replaced at least once every 24 hours.

Use only if solution is clear and container and seals are intact.

Parenteral drug products should be inspected visually for particulate matter and discoloration prior to administration whenever solution and container permit.

If administration is by pressure infusion, all air should be withdrawn or expelled from the bag through the medication port prior to infusion.

The safety and compatibility of other additives have not been established. This product contains calcium and should not be administered simultaneously with blood through the same administration set because of the likelihood of coagulation (see WARNINGS AND PRECAUTIONS).

The solution contains no bacteriostat or antimicrobial agent and is intended only for single-dose injection. When smaller doses are required, the unused portion should be discarded.

HOW SUPPLIED

HEXTEND (6% Hetastarch in Lactated Electrolyte Injection) is supplied sterile and nonpyrogenic in 500 mL single-dose flexible plastic infusion containers.

Unit of Sale | Volume/Container | Each
NDC 0409-1555-54; Case containing 12 | 500 mL | NDC 0409-1555-64; Single-dose Flexible Container

Exposure of pharmaceutical products to heat should be minimized. Avoid excessive heat. Protect from freezing. It is recommended that the product be stored at room temperature (25°C/77°F); however, brief exposure up to 40°C does not adversely affect the product.

References:

1. Diehl J, et al., Clinical Comparison of Hetastarch and Albumin in Postoperative Cardiac Patients. The Annals of Thoracic Surgery, 1982;34(6):674-679.
2. Gold M, et al., Comparison of Hetastarch to Albumin for Perioperative Bleeding in Patients Undergoing Abdominal Aortic Aneurysm Surgery, Annals of Surgery, 1990;211(4):482-485.
3. Kirklin J, et al., Hydroxyethyl Starch versus Albumin for Colloid Infusion Following Cardiopulmonary Bypass in Patients Undergoing Myocardial Revascularization, The Annals of Thoracic Surgery, 1984;37(1):40-46.
4. Moggio RA, et al., Hemodynamic Comparison of Albumin and Hydroxyethyl Starch in Postoperative Cardiac Surgery Patients, Critical Care Medicine, 1983;11(12):943-945.
5. Knutson, JE, et al., Does Intraoperative Hetastarch Administration Increase Blood Loss and Transfusion Requirements After Cardiac Surgery? Anesthesia Analg., 2000;90: 801-7.
6. Cope, JT, et al., Intraoperative Hetastarch Infusion Impairs Hemostasis After Cardiac Operations, The Annals of Thoracic Surgery, 1997;63: 78-83.
7. Damon L, Intracranial Bleeding During Treatment with Hydroxyethyl Starch, New England Journal of Medicine, 1987; 317(15):964-965.
8. Brutocao D, et al., Comparison of Hetastarch with Albumin for Postoperative Volume Expansion in Children After Cardiopulmonary Bypass, Journal of Cardiothoracic and Vascular Anesthesia, 1996;10(3):348-351.
9. Perner A, Haase N, Guttormsen AB, et al. Hydroxyethyl Starch 130/0.42 versus Ringer's Acetate in Severe Sepsis. N Eng J Med 2012; 367(2): 124-34
10. CRYSTMAS: Guidet B, Martinet O, Boulain T, et al. Assessment of hemodynamic efficacy and safety of 6% hydroxyethylstarch 130/0.4 versus 0.9% NaCl fluid replacement in patients with severe sepsis: The CRYSTMAS study. Crit Care 2012; 16(3): R94
11. Myburgh JA, Finfer S, Bellomo R, et al. Hydroxyethyl starch or saline for fluid resuscitation in intensive care. N Engl J Med 2012; 367(20): 1901-11
12. Ahn HJ, Kim JA, Lee AR, et al. The risk of acute kidney injury from fluid restriction and hydroxyethyl starch in thoracic surgery. Anesth Analg 2016; 122(1):186–193.
13. Green RS, Butler MB, Hicks SD, et al. Effect of hydroxyethyl starch on outcomes in high-risk vascular surgery patients: A retrospective analysis. J Cardiothorac Vasc Anesth 2016; 30(4):967–72.
14. Kashy BK, Podolyak A, Makarova N, et al. Effect of hydroxyethyl starch on postoperative kidney function in patients having noncardiac surgery. Anesthesiology 2014; 121 (4):730–9.
15. Patel MS, Niemann CU, Sally MB, et al. The impact of hydroxyethyl starch use in deceased organ donors on the development of delayed graft function in kidney transplant recipients: A Propensity-Adjusted Analysis. Am J of Transplant 2015; 15 (8):2152–8.
16. Rasmussen KC, Johansson PI, Højskov M, et al. Hydroxyethyl starch reduces coagulation competence and increases blood loss during major surgery: results from a randomized controlled trial. Ann Surg 2014; 259 (2):249–54.
17. Bayer O, Schwarzkopf D, Doenst T, et al. Perioperative fluid therapy with tetrastarch and gelatin in cardiac surgery – a prospective sequential analysis. Crit Care Med 2013; 41(11):2532–42.
18. Lagny MG, Roediger L, Koch JN, et al. Hydroxyethyl starch 130/0.4 and the risk of acute kidney injury after cardiopulmonary bypass: A single-center retrospective study. J of Cardiothorac and Vasc Anesth 2016: 30(4):869–75.
19. Wilkes MM, Navickis RJ. Postoperative renal replacement therapy after hydroxyethyl starch infusion: a meta-analysis of randomized trials. Neth J Crit Care 2014; 18:4–9.
20. Allen CJ, Valle EJ, Jouria JM, et al. Differences between blunt and penetrating trauma after resuscitation with HES. J Trauma Acute Care Surg 2014; 77(6):859–64.
21. Eriksson M, Brattström O, Mårtensson J, et al. Acute kidney injury following severe trauma: Risk factors and long-term outcome. J Trauma Acute Care Surg 2015; 79(3):407–12.

To Open

Tear overwrap down at notch and remove solution container. Check for any leakage by squeezing solution container firmly. If leaks are found, discard solution as sterility may be impaired.

Invert container and carefully inspect the solution in good light for cloudiness, haze, or particulate matter. Any container that is suspect should not be used.

Distributed by: Hospira, Inc., Lake Forest, IL 60045 USA

LAB-1288-3.0

Revised: 1/2026

PRINCIPAL DISPLAY PANEL - 500 mL Bag

500 mL
HEXTEND®
6% Hetastarch in
Lactated Electrolyte Injection
NDC 0409-1555-64

FOR INTRAVENOUS USE ONLY
RX ONLY

EACH 100 mL CONTAINS: 6 g HETASTARCH, 672 mg SODIUM
CHLORIDE, USP, 317 mg SODIUM LACTATE ANHYDROUS, USP, 99 mg
DEXTROSE HYDROUS, USP, 37 mg CALCIUM CHLORIDE DIHYDRATE,
USP, 22 mg POTASSIUM CHLORIDE, USP, 9 mg MAGNESIUM
CHLORIDE HEXAHYDRATE, USP, IN WATER FOR INJECTION, USP. pH:
APPROX. 5.9 WITH NEGLIGIBLE BUFFERING CAPACITY.
ELECTROLYTES (mEq/L): SODIUM 143, CHLORIDE 124, LACTATE 28,
CALCIUM 5, POTASSIUM 3, MAGNESIUM 0.9. CALCULATED
OSMOLARITY: APPROX 307 mOsM. DO NOT INTRODUCE ADDITIVES
INTO THIS CONTAINER OR USE IN SERIES CONNECTIONS WITH
BLOOD OR BLOOD PRODUCTS. IF ADMINISTRATION IS BY PRESSURE
INFUSION, ALL AIR SHOULD BE WITHDRAWN OR EXPELLED FROM
THE BAG THROUGH THE MEDICATION PORT PRIOR TO INFUSION.
CHECK FOR ANY LEAKAGE BY SQUEEZING CONTAINER FIRMLY. IF
ANY LEAKS ARE FOUND, DISCARD SOLUTION AS STERILITY MAY BE
IMPAIRED. STERILE, NONPYROGENIC. SINGLE-DOSE CONTAINER.
DISCARD UNUSED PORTION. USE ONLY IF SOLUTION IS CLEAR AND
CONTAINER AND SEAL ARE INTACT. RECOMMENDED STORAGE:
ROOM TEMPERATURE 25°C (77°F). AVOID EXCESSIVE HEAT.
PROTECT FROM FREEZING. USUAL DOSAGE: SEE PACKAGE
INSERT FOR COMPLETE INFORMATION.
DISTRIBUTED BY HOSPIRA, INC.
LAKE FOREST, IL 60045 USA.
Hospira

3
V
CONTAINS DEHP

14616700
IM-4486

PRINCIPAL DISPLAY PANEL - 500 mL Overwrap Label

TO OPEN TEAR AT NOTCH

DO NOT REMOVE FROM OVERWRAP UNTIL READY FOR USE. AFTER REMOVING
THE OVERWRAP, CHECK FOR MINUTE LEAKS BY SQUEEZING CONTAINER
FIRMLY. IF LEAKS ARE FOUND, DISCARD SOLUTION AS STERILITY MAY BE
IMPAIRED. RECOMMENDED STORAGE: ROOM TEMPERATURE (25°C). AVOID
EXCESSIVE HEAT. PROTECT FROM FREEZING. SEE INSERT.
IM-4498

2
HDPE

Not Made With Natural Rubber Latex

14622100